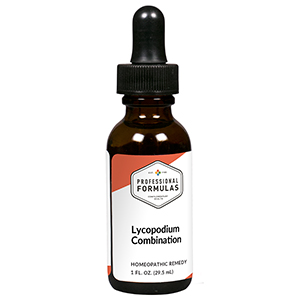 DRUG LABEL: Lycopodium Combination
NDC: 63083-9231 | Form: LIQUID
Manufacturer: Professional Complementary Health Formulas
Category: homeopathic | Type: HUMAN OTC DRUG LABEL
Date: 20190815

ACTIVE INGREDIENTS: MILK THISTLE 2 [hp_X]/29.5 mL; CINCHONA OFFICINALIS BARK 3 [hp_X]/29.5 mL; LYCOPODIUM CLAVATUM SPORE 3 [hp_X]/29.5 mL; CHELIDONIUM MAJUS WHOLE 4 [hp_X]/29.5 mL; NUTMEG 4 [hp_X]/29.5 mL; CITRULLUS COLOCYNTHIS FRUIT PULP 6 [hp_X]/29.5 mL; PHOSPHORUS 6 [hp_X]/29.5 mL; VERATRUM ALBUM ROOT 6 [hp_X]/29.5 mL; BEEF LIVER 8 [hp_X]/29.5 mL; BOS TAURUS DUODENUM 10 [hp_X]/29.5 mL; BOS TAURUS GALLBLADDER 10 [hp_X]/29.5 mL; BOS TAURUS PANCREAS 10 [hp_X]/29.5 mL; HYSSOPUS OFFICINALIS WHOLE 10 [hp_X]/29.5 mL; BOS TAURUS COLON 12 [hp_X]/29.5 mL; HEPATITIS A VIRUS STRAIN HM175 ANTIGEN (FORMALDEHYDE INACTIVATED) 14 [hp_X]/29.5 mL
INACTIVE INGREDIENTS: ALCOHOL; WATER

R231

ACTIVE INGREDIENTS

Carduus marianus 2X
Cinchona officinalis 3X
Lycopodium clavatum 3X
Chelidonium majus 4X
Nux moschata 4X
Colocynthis 6X
Phosphorus 6X
Veratrum album 6X
Liver 8X
Duodenum 10X
Gallbladder 10X
Pancreas 10X
Thymus 10X
Colon 12X
Hepatitis 14X

QUESTIONS

Professional Formulas

PO Box 2034 Lake Oswego, OR 97035

INDICATIONS

For the temporary relief of loss of appetite, minor abdominal pain, nausea, or vomiting.*

PURPOSE

*Claims based on traditional homeopathic practice, not accepted medical evidence. Not FDA evaluated.

WARNINGS

If symptoms do not improve or are accompanied by a fever, consult a doctor. Keep out of the reach of children. In case of overdose, get medical help or contact a poison control center right away. If pregnant or breastfeeding, ask a healthcare professional before use.

Keep out of the reach of children.

PREGNANCY OR BREAST FEEDING

If pregnant or breastfeeding, ask a healthcare professional before use.

DIRECTIONS

Place drops under tongue 30 minutes before/after meals. Adults and children 12 years and over: Take 10 drops up to 3 times per day. Consult a physician for use in children under 12 years of age.

OTHER INFORMATION

Tamper resistant. If seal is broken, do not use. After opening, close container tightly and store at room temperature away from heat.

INACTIVE INGREDIENTS

40% ethanol, purified water.

LABEL

Est 1985

Professional Formulas

Complementary Health

Lycopodium Combination

Homeopathic Remedy

1 FL. OZ. (29.5 mL)